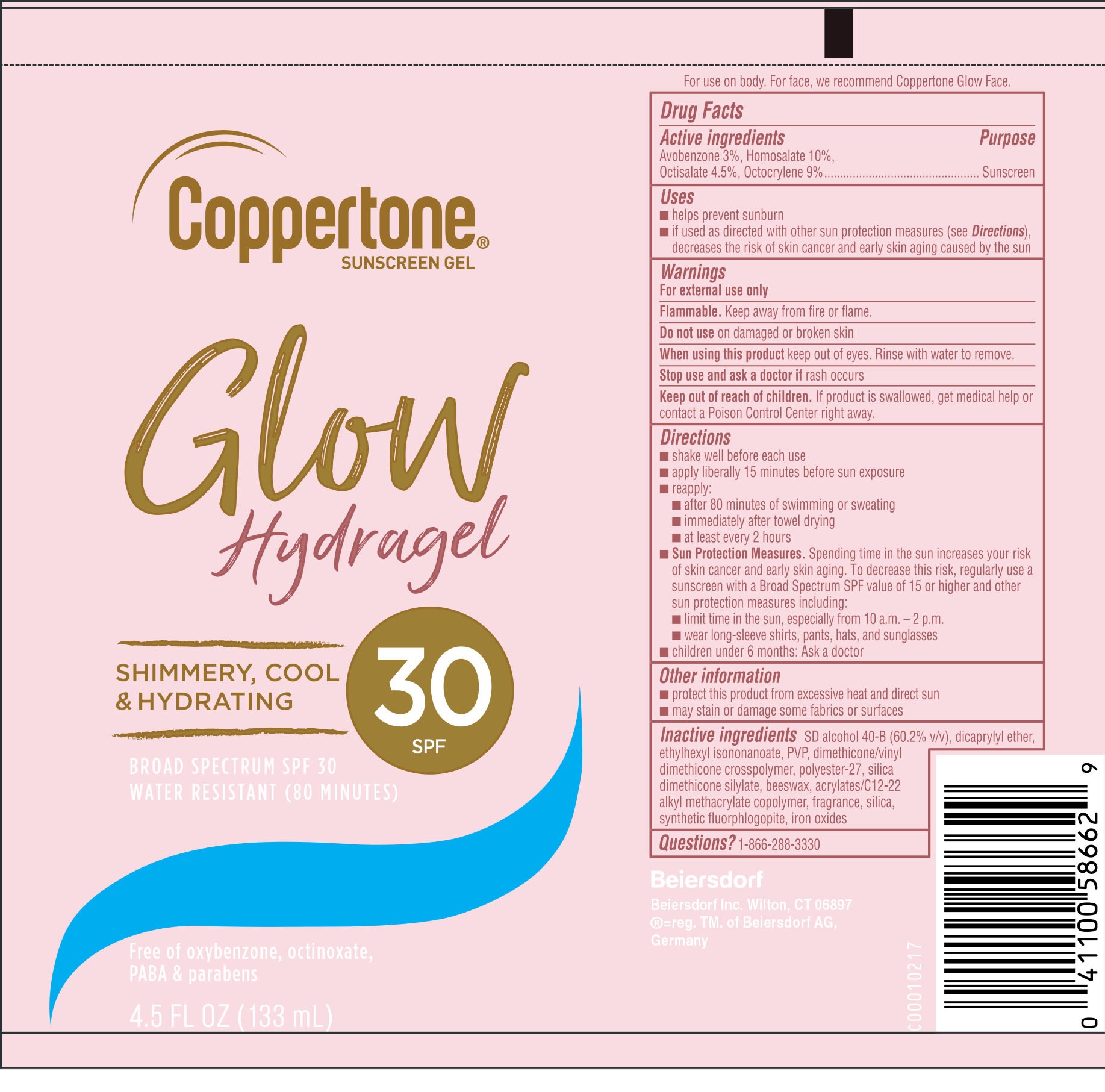 DRUG LABEL: Coppertone Glow Hydragel Sunscreen SPF 30
NDC: 66800-4480 | Form: GEL
Manufacturer: Beiersdorf Inc
Category: otc | Type: HUMAN OTC DRUG LABEL
Date: 20251231

ACTIVE INGREDIENTS: HOMOSALATE 100 mg/1 mL; OCTISALATE 45 mg/1 mL; AVOBENZONE 30 mg/1 mL; OCTOCRYLENE 90 mg/1 mL
INACTIVE INGREDIENTS: MODIFIED CORN STARCH (1-OCTENYL SUCCINIC ANHYDRIDE); DIMETHICONE/VINYL DIMETHICONE CROSSPOLYMER (HARD PARTICLE); POLYESTER-7; FERRIC OXIDE RED; POVIDONE, UNSPECIFIED; STARCH, CORN; ALUMINUM MAGNESIUM HYDROXIDE CARBONATE; FRAGRANCE FRESH CITRUS FLORAL ORC1501495; OCTENYLSUCCINIC ACID; SILICA DIMETHYL SILYLATE; ALCOHOL; DICAPRYLYL ETHER; ETHYLHEXYL ISONONANOATE; BUTYLOCTYL SALICYLATE; BUTYL ACRYLATE/C16-C20 ALKYL METHACRYLATE/METHACRYLIC ACID/METHYL METHACRYLATE COPOLYMER

Glow Hydragel Sunscreen SPF 30

Drug Facts

Active ingredients

Avobenzone 3%, Homosalate 10%, Octisalate 4.5%, Octocrylene 9%

Purpose

Sunscreen

Uses

■ helps prevent sunburn

■ if used as directed with other sun protection measures (see Directions), decreases the risk of skin cancer and early skin aging caused by the sun

Warnings

For external use only

Flammable.Keep away from fire or flame.

Do not useon damaged or broken skin

WHEN USING

When using this productkeep out of eyes. Rinse with water to remove.

Stop use and ask a doctor ifrash occurs

Keep out of reach of children.If product is swallowed, get medical help or contact a Poison Control Center right away.

Directions

■ shake well before each use

■ apply liberally 15 minutes before sun exposure

■ reapply:

■ after 80 minutes of swimming or sweating

■ immediately after towel drying

■ at least every 2 hours

■ Sun Protection Measures.Spending time in the sun increases your risk of skin cancer and early skin aging. To decrease this risk, regularly use a sunscreen with a Broad Spectrum SPF value of 15 or higher and other sun protection measures including:

■ limit time in the sun, especially from 10 a.m. – 2 p.m.

■ wear long-sleeve shirts, pants, hats, and sunglasses

■ children under 6 months: Ask a doctor

Other Information

■ protect this product from excessive heat and direct sun

■ may stain or damage some fabrics or surfaces

Inactive ingredients

SD alcohol 40-B (60.2% v/v), dicaprylyl ether, ethylhexyl isononanoate, PVP, dimethicone/vinyl dimethicone crosspolymer, polyester-27, silica dimethicone silylate, beeswax, acrylates/C12-22 alkyl methacrylate copolymer, fragrance, silica, synthetic fluorphlogopite, iron oxides

Questions

1-866-288-3330

PACKAGE LABEL

Coppertone Sunscreen Gel

Glow Hydragel

SPF 30

Shimmery, Cool & Hydrating

Broad Spectrum SPF 30

Water Resistant (80 Minutes)

Free of oxybenzone, octinoxate, PABA & parabens

4.5 FL OZ (133 mL)